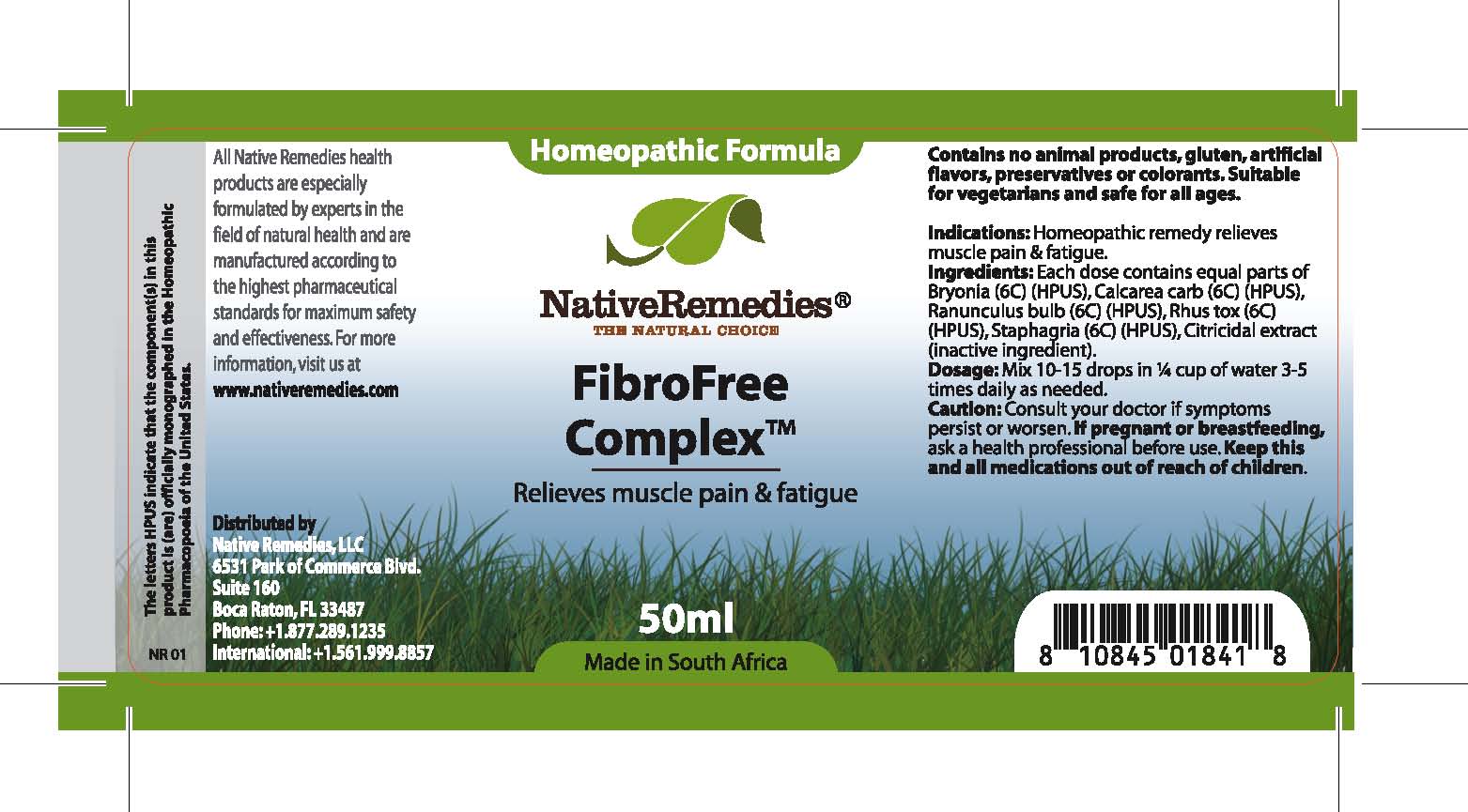 DRUG LABEL: FibroFree Complex
NDC: 68647-197 | Form: TINCTURE
Manufacturer: Feelgood Health
Category: homeopathic | Type: HUMAN OTC DRUG LABEL
Date: 20100817

ACTIVE INGREDIENTS: BRYONIA ALBA ROOT 6 [hp_C]/40 mL; OYSTER SHELL CALCIUM CARBONATE, CRUDE 6 [hp_C]/40 mL; RANUNCULUS BULBOSUS 6 [hp_C]/40 mL; TOXICODENDRON PUBESCENS LEAF 6 [hp_C]/40 mL; DELPHINIUM STAPHISAGRIA SEED 6 [hp_C]/40 mL
INACTIVE INGREDIENTS: CITRUS PARADISI SEED 0.03 mL/50 mL; WATER 98.97 mL/50 mL

FIBROFREE COMPLEX

PURPOSE

Relieves muscle pain and fatigue

Indications: Homeopathic remedy relieves muscle pain and fatigue.

DOSAGE AND ADMINISTRATION

Dosage: Mix 10-15 drops in ¼ cup of water 3-5 times daily as needed.

GENERAL PRECAUTIONS

Caution: Consult your doctor if symptoms persist or worsen. Keep this and all medications out of reach of children.

ACTIVE INGREDIENT

Ingredients: Each dose contains equal parts of Bryonia (6C) (HPUS), Calcarea carb (6C) (HPUS), Ranunculus bulb (6C) (HPUS), Rhus tox (6C) (HPUS), Staphagria (6C) (HPUS)

Citricidal Extract (inactive ingredient).

PREGNANCY

If pregnant or breastfeeding, ask a health professional before use.

WARNINGS

Contains no animal products, gluten, artificial flavors, preservatives or colorants. Suitable for vegetarians and safe for all ages.

PATIENT COUNSELING INFORMATION

All Native Remedies health products are especially formulated by experts in the field of natural health and are manufactured according to the highest pharmaceutical standards for maximum safety and effectiveness. For more information, visit us at www.nativeremedies.com

Distributed by

Native Remedies, LLC

6531 Park of Commerce Blvd.

Suite 160

Boca Raton, FL 33487

Phone: 1.877.289.1235

International: + 1.561.999.8857

The letters HPUS indicate that the component(s) in this product is (are) officially monographed in the Homeopathic Pharmacopoeia of the United States.

KEEP OUT OF REACH OF CHILDREN

Keep this and all medications out of reach of children.